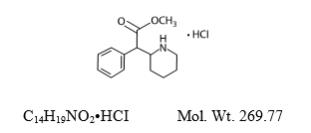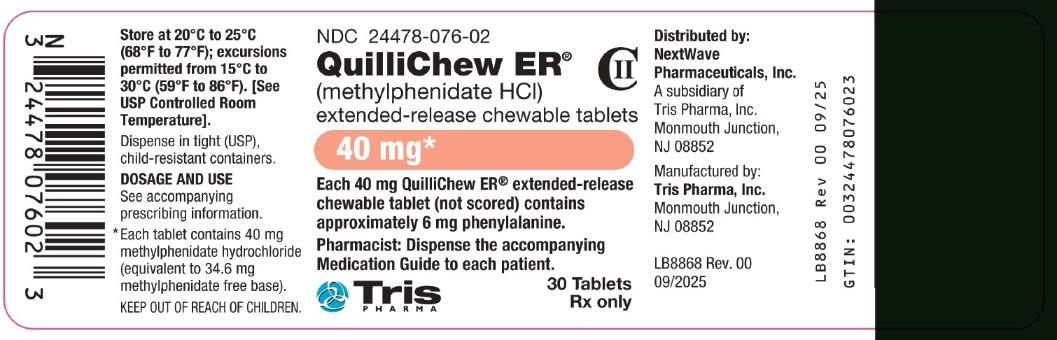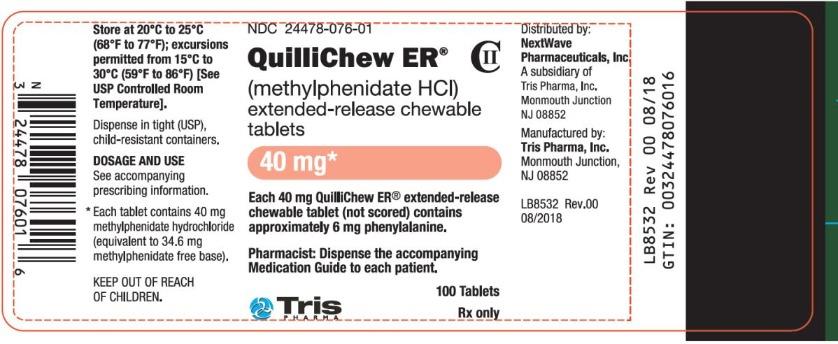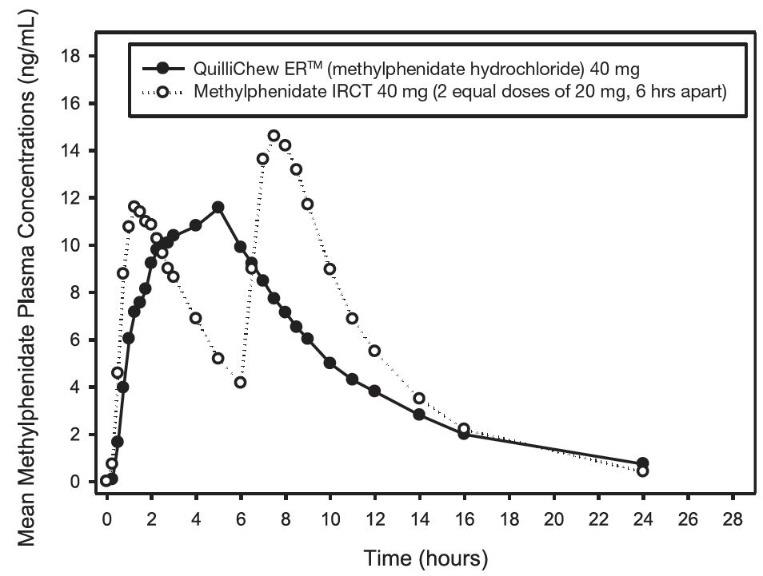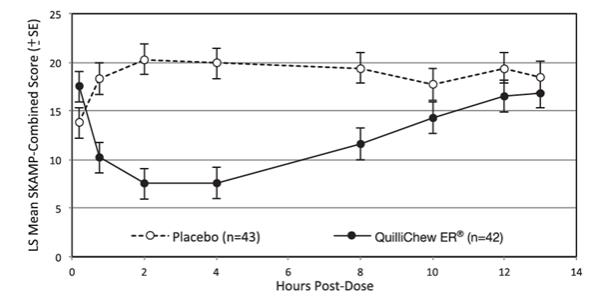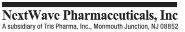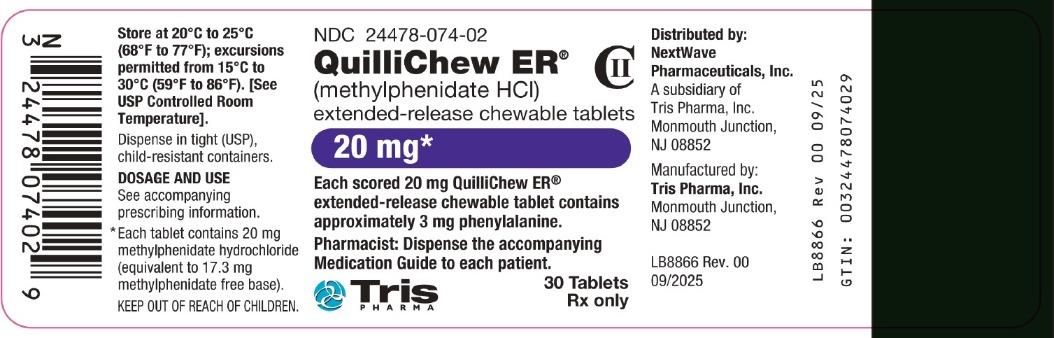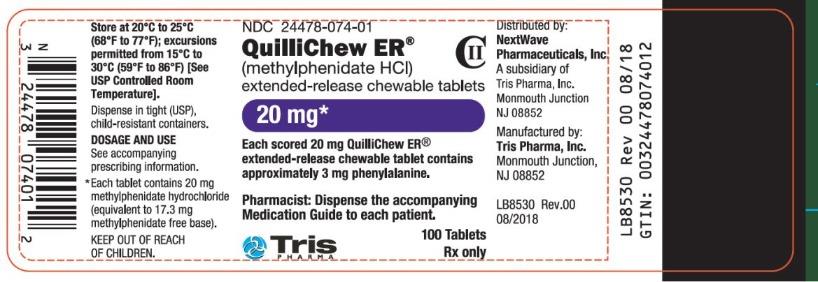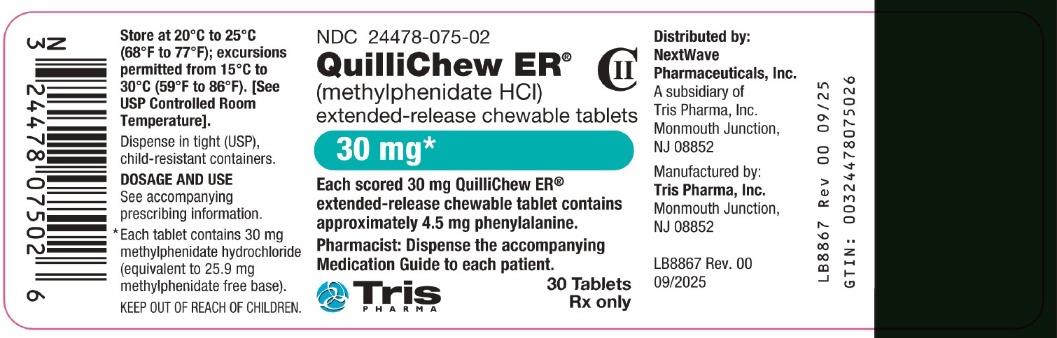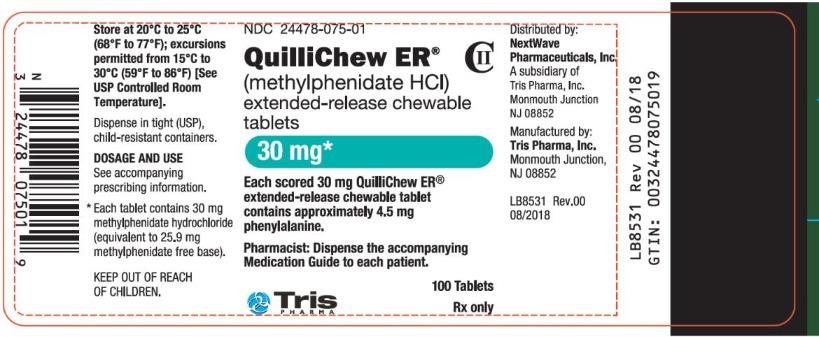 DRUG LABEL: QuilliChew ER
NDC: 24478-074 | Form: TABLET, CHEWABLE, EXTENDED RELEASE
Manufacturer: NextWave Pharmaceuticals, Inc
Category: prescription | Type: HUMAN PRESCRIPTION DRUG LABEL
Date: 20260225
DEA Schedule: CII

ACTIVE INGREDIENTS: METHYLPHENIDATE HYDROCHLORIDE 20 mg/1 1
INACTIVE INGREDIENTS: SODIUM POLYSTYRENE SULFONATE; TRIACETIN; XANTHAN GUM; TALC; SILICON DIOXIDE; ASPARTAME; CHERRY; CITRIC ACID MONOHYDRATE; CROSPOVIDONE (15 MPA.S AT 5%); GUAR GUM; MAGNESIUM STEARATE; MANNITOL; MICROCRYSTALLINE CELLULOSE; POLYVINYL ACETATE; POLYVINYL ALCOHOL, UNSPECIFIED; POVIDONE, UNSPECIFIED

HIGHLIGHTS OF PRESCRIBING INFORMATION

These highlights do not include all the information needed to use QUILLICHEW ER® safely and effectively. See full prescribing information for QUILLICHEW ER®.
QUILLICHEW ER® (methylphenidate hydrochloride) extended-release chewable tablets, for oral use, CII
Initial U.S. Approval: 1955

WARNING: ABUSE, MISUSE AND ADDICTION

See full prescribing information for complete boxed warning.

QUILLICHEW ER has a high potential for abuse and misuse, which can lead to the development of a substance use disorder, including addiction. Misuse and abuse of CNS stimulants, including QUILLICHEW ER, can result in overdose and death (5.1, 9.2, 10):

- Before prescribing QUILLICHEW ER, assess each patient’s risk for abuse, misuse, and addiction.
- Educate patients and their families about these risks, proper storage of the drug, and proper disposal of any unused drug.
- Throughout treatment, reassess each patient’s risk and frequently monitor for signs and symptoms of abuse, misuse, and addiction.

RECENT MAJOR CHANGES

Indications and Usage (1) 09/2025

Warnings and Precautions (5.7) 09/2025

1 INDICATIONS AND USAGE

QuilliChew ER is a central nervous system (CNS) stimulant indicated for the treatment of Attention Deficit Hyperactivity Disorder (ADHD). (1)

Limitations of Use

The use of QuilliChew ER is not recommended in pediatric patients younger than 6 years of age because they had higher plasma exposure and a higher incidence of adverse reactions (e.g., weight loss) than patients 6 years and older at the same dosage (5.7, 8.4).

2 DOSAGE AND ADMINISTRATION

- QuilliChew ER may be taken with or without food. (2.1)
- For patients 6 years and above, recommended starting dose is 20 mg given orally once daily in the morning. Dosage may be titrated weekly in increments of 10 mg, 15 mg or 20 mg per day. Daily dosage above 60 mg is not recommended. (2.1)

3 DOSAGE FORMS AND STRENGTHS

- Extended-release chewable tablets: 20 mg and 30 mg of methylphenidate hydrochloride (HCl), functionally scored (3)
- Extended-release chewable tablets: 40 mg of methylphenidate HCl, not scored (3)

4 CONTRAINDICATIONS

- Known hypersensitivity to methylphenidate or product components. (4.1)
- Concurrent treatment with a monoamine oxidase inhibitor (MAOI), or use of an MAOI within the preceding 14 days. (4.2, 7.1)

5 WARNINGS AND PRECAUTIONS

- Risks to Patients with Serious Cardiac Disease: Avoid use in patients with known structural cardiac abnormalities, cardiomyopathy, serious cardiac arrhythmias, coronary artery disease, or other serious cardiac disease. (5.2)
- Increased Blood Pressure and Heart Rate: Monitor blood pressure and pulse. (5.3)
- Psychiatric Adverse Reactions: Prior to initiating QuilliChew ER, screen patients for risk factors for developing a manic episode. If new psychotic or manic symptoms occur, consider discontinuing QuilliChew ER. (5.4)
- Priapism: If abnormally sustained or frequent and painful erections occur, patients should seek immediate medical attention. (5.5)
- Peripheral Vasculopathy, including Raynaud’s Phenomenon: Careful observation for digital changes is necessary during QuilliChew ER treatment. Further clinical evaluation (e.g., rheumatology referral) may be appropriate for patients who develop signs or symptoms of peripheral vasculopathy. (5.6)
- Long-Term Suppression of Growth in Pediatric Patients: Closely monitor growth (height and weight) in pediatric patients. Pediatric patients not growing or gaining height or weight as expected may need to have their treatment interrupted. (5.7)
- Risks in Phenylketonurics: QuilliChew ER extended-release chewable tablets contain phenylalanine, a component of aspartame. (5.8)
- Acute Angle Closure Glaucoma: QuilliChew ER -treated patients considered at risk for acute angle closure glaucoma (e.g., patients with significant hyperopia) should be evaluated by an ophthalmologist. (5.9)
- Increased Intraocular Pressure (IOP) and Glaucoma: Prescribe QuilliChew ER to patients with open-angle glaucoma or abnormally increased IOP only if the benefit of treatment is considered to outweigh the risk. Closely monitor patients with a history of increased IOP or open angle glaucoma. (5.10)
- Motor and Verbal Tics, and Worsening of Tourette’s Syndrome: Before initiating QuilliChew ER, assess the family history and clinically evaluate patients for tics or Tourette’s syndrome. Regularly monitor patients for the emergence or worsening of tics or Tourette’s syndrome. Discontinue treatment if clinically appropriate. (5.11)

6 ADVERSE REACTIONS

Based on accumulated data from other methylphenidate products, the most common (≥5% and twice the rate of placebo) adverse reactions are appetite decreased, insomnia, nausea, vomiting, dyspepsia, abdominal pain, weight decreased, anxiety, dizziness, irritability, affect lability, tachycardia, and blood pressure increased. (6.1)

To report SUSPECTED ADVERSE REACTIONS, contact Tris Pharma, Inc. at (732) 940-0358 or FDA at 1-800-FDA-1088 or www.fda.gov/medwatch.

7 DRUG INTERACTIONS

- Antihypertensive Drugs: Monitor blood pressure. Adjust dosage of antihypertensive drug as needed. (7)

FULL PRESCRIBING INFORMATION

WARNING: ABUSE, MISUSE AND ADDICTION

QuilliChew ER has a high potential for abuse and misuse, which can lead to the development of a substance use disorder, including addiction. Misuse and abuse of CNS stimulants, including QuilliChew ER, can result in overdose and death [see Overdosage (10)], and this risk is increased with higher doses or unapproved methods of administration, such as snorting or injection.
Before prescribing QuilliChew ER, assess each patient’s risk for abuse, misuse, and addiction. Educate patients and their families about these risks, proper storage of the drug, and proper disposal of any unused drug. Throughout QuilliChew ER treatment, reassess each patient’s risk of abuse, misuse, and addiction and frequently monitor for signs and symptoms of abuse, misuse, and addiction [see Warnings and Precautions (5.1) and Drug Abuse and Dependence (9.2)].

1 INDICATIONS AND USAGE

QuilliChew ER is indicated for the treatment of Attention Deficit Hyperactivity Disorder (ADHD) [see Clinical Studies (14)].

Limitations of Use

The use of QuilliChew ER is not recommended in pediatric patients younger than 6 years of age because they had higher plasma exposure and a higher incidence of adverse reactions (e.g., weight loss) than patients 6 years and older at the same dosage [see Warnings and Precautions (5.7), Use in Specific Populations (8.4)].

2 DOSAGE AND ADMINISTRATION

2.1 Pretreatment Screening

Prior to treating patients with QuilliChew ER, assess:

- for the presence of cardiac disease (i.e., perform a careful history, family history of sudden death or ventricular arrhythmia, and physical exam) [see Warnings and Precautions (5.2)].
- the family history and clinically evaluate patients for motor or verbal tics or Tourette’s syndrome before initiating QuilliChew ER [see Warnings and Precautions (5.10)].

2.2 Recommended Dosage

The recommended starting dosage of QuilliChew ER for patients 6 years and above is 20 mg once daily orally in the morning. The dose may be titrated up or down weekly in increments of 10 mg, 15 mg or 20 mg. The 10 mg and 15 mg doses can each be achieved by breaking in half the functionally scored 20 mg and 30 mg tablets, respectively. Daily doses above 60 mg have not been studied and are not recommended. As with any CNS stimulant, during titration of QuilliChew ER, the prescribed dose should be adjusted, if necessary, until a well-tolerated, therapeutic dose is achieved.

2.3 Administration Instructions

QuilliChew ER should be orally administered once daily in the morning with or without food [see Clinical Pharmacology (12.3)].

2.4 Switching from other Methylphenidate Products

If switching from other methylphenidate products, discontinue that treatment, and titrate with QuilliChew ER using the above titration schedule.

Do not substitute for other methylphenidate products on a milligram-per-milligram basis, because of different methylphenidate base compositions and differing pharmacokinetic profiles [see Description (11), Clinical Pharmacology (12.3)].

2.5 Dosage Reduction and Discontinuation

If paradoxical aggravation of symptoms or other adverse reaction occur, reduce dosage, or, if necessary, discontinue QuilliChew ER. If improvement is not observed after appropriate dosage adjustment over a one-month period, discontinue QuilliChew ER.

3 DOSAGE FORMS AND STRENGTHS

Extended-release chewable tablets:

20 mg equivalent of methylphenidate HCl available as a speckled, off-white, capsule-shaped coated tablet, debossed with "NP 12" on one side and functionally scored on the other side.

30 mg equivalent of methylphenidate HCl available as a speckled, light pink color, capsule-shaped coated tablet, debossed with "NP 13" on one side and functionally scored on the other side.

40 mg equivalent of methylphenidate HCl available as a speckled, dark pink to peach color, capsule-shaped coated tablet, debossed with "NP 14" on one side and plain (not scored) on the other side.

4 CONTRAINDICATIONS

4.1 Hypersensitivity to Methylphenidate or other Components of QuilliChew ER

QuilliChew ER is contraindicated in patients known to be hypersensitive to methylphenidate, or other components of QuilliChew ER. Hypersensitivity reactions such as angioedema and anaphylactic reactions have been reported in patients treated with other methylphenidate products [see Adverse Reactions (6.2)].

4.2 Monoamine Oxidase Inhibitors

QuilliChew ER is contraindicated during concomitant treatment with monoamine oxidase inhibitors (MAOIs), and also within 14 days following discontinuation of treatment with a monoamine oxidase inhibitor (MAOI), because of the risk of hypertensive crisis [see Drug Interactions (7.1)].

5 WARNINGS AND PRECAUTIONS

5.1 Abuse, Misuse, and Addiction

QuilliChew ER has a high potential for abuse and misuse. The use of QuilliChew ER exposes individuals to the risks of abuse and misuse, which can lead to the development of a substance use disorder, including addiction. QuilliChew ER can be diverted for non-medical use into illicit channels or distribution [see Drug Abuse and Dependence (9.2)]. Misuse and abuse of CNS stimulants, including QuilliChew ER, can result in overdose and death [see Overdosage (10)], and this risk is increased with higher doses or unapproved methods of administration, such as snorting or injection.

Before prescribing QuilliChew ER, assess each patient’s risk for abuse, misuse, and addiction.

Educate patients and their families about these risks and proper disposal of any unused drug. Advise patients to store QuilliChew ER in a safe place, preferably locked, and instruct patients to not give QuilliChew ER to anyone else. Throughout QuilliChew ER treatment, reassess each patient’s risk of abuse, misuse, and addiction and frequently monitor for signs and symptoms of abuse, misuse, and addiction.

5.2 Risks to Patients with Serious Cardiac Disease

Sudden death has occurred in patients with structural cardiac abnormalities or other serious cardiac disease who were treated with CNS stimulants at the recommended ADHD dosage.

Avoid QuilliChew ER use in patients with known structural cardiac abnormalities, cardiomyopathy, serious cardiac arrhythmias, coronary artery disease, or other serious cardiac disease.

5.3 Increased Blood Pressure and Heart Rate

CNS stimulants cause an increase in blood pressure (mean increase approximately 2 to 4 mmHg) and heart rate (mean increase approximately 3 to 6 bpm). Some patients may have larger increases.

Monitor all QuilliChew ER-treated patients for hypertension and tachycardia.

5.4 Psychiatric Adverse Reactions

Exacerbation of Pre-existing Psychosis

CNS stimulants may exacerbate symptoms of behavior disturbance and thought disorder in patients with a pre-existing psychotic disorder.

Induction of a Manic Episode in Patients with Bipolar Disorder

CNS stimulants may induce a manic or mixed episode in patients. Prior to initiating QuilliChew ER treatment, screen patients for risk factors for developing a manic episode (e.g., comorbid or history of depressive symptoms or a family history of suicide, bipolar disorder, or depression).

New Psychotic or Manic Symptoms

CNS stimulants, at the recommended dosage, may cause psychotic or manic symptoms (e.g., hallucinations, delusional thinking, or mania) in patients without a prior history of psychotic illness or mania. In a pooled analysis of multiple short-term, placebo-controlled studies of CNS stimulants, psychotic or manic symptoms occurred in approximately 0.1% of CNS stimulant-treated patients, compared to 0% of placebo-treated patients. If such symptoms occur, consider discontinuing QuilliChew ER.

5.5 Priapism

Prolonged and painful erections, sometimes requiring surgical intervention, have been reported with methylphenidate use in both adult and pediatric male patients. Although priapism was not reported with methylphenidate initiation, it developed after some time on methylphenidate, often subsequent to an increase in dosage. Priapism also occurred during a period of methylphenidate withdrawal (drug holidays or during discontinuation).
QuilliChew ER treated patients who develop abnormally sustained or frequent and painful erections should seek immediate medical attention.

5.6 Peripheral Vasculopathy, including Raynaud’s Phenomenon

CNS stimulants, including QuilliChew ER, used to treat ADHD are associated with peripheral vasculopathy, including Raynaud's phenomenon. Signs and symptoms are usually intermittent and mild; however, sequelae have included digital ulceration and/or soft tissue breakdown. Effects of peripheral vasculopathy, including Raynaud's phenomenon, were observed in post-marketing reports and at the therapeutic dosages of CNS stimulants in all age groups throughout the course of treatment. Signs and symptoms generally improved after dosage reduction or discontinuation of the CNS stimulant.

Careful observation of digital changes is necessary during QuilliChew ER treatment. Further clinical evaluation (e.g., rheumatology referral) may be appropriate for QuilliChew ER-treated patients who develop signs or symptoms of peripheral vasculopathy.

5.7 Long-Term Suppression of Growth in Pediatric Patients

QuilliChew ER is not approved for use and is not recommended in pediatric patients below 6 years of age [see Use in Specific Populations (8.4)].

CNS stimulants have been associated with weight loss and slowing of growth rate in pediatric patients.

Careful follow-up of weight and height in pediatric patients ages 7 to 10 years who were randomized to either methylphenidate or nonmedication treatment groups over 14 months, as well as in naturalistic subgroups of newly methylphenidate-treated and nonmedication-treated pediatric patients over 36 months (to the ages of 10 to 13 years), suggests that pediatric patients who received methylphenidate for 7 days per week throughout the year had a temporary slowing in growth rate (on average, a total of about 2 cm less growth in height and 2.7 kg less growth in weight over 3 years), without evidence of growth rebound during this development period.

Closely monitor growth (weight and height) in QuilliChew ER-treated pediatric patients. Pediatric patients who are not growing or gaining height or weight as expected may need to have their treatment interrupted.

5.8 Risks in Patients with Phenylketonuria

Phenylalanine can be harmful to patients with phenylketonuria (PKU). QuilliChew ER extended-release chewable tablets contain phenylalanine, a component of aspartame. Each 20 mg, 30 mg, and 40 mg extended-release chewable tablet contains 3 mg, 4.5 mg, and 6 mg phenylalanine, respectively. Before prescribing QuilliChew ER in patients with PKU, consider the combined daily amount of phenylalanine from all sources, including QuilliChew ER.

5.9 Acute Angle Closure Glaucoma

There have been reports of angle closure glaucoma associated with methylphenidate treatment.

Although the mechanism is not clear, QuilliChew ER -treated patients considered at risk for acute angle closure glaucoma (e.g., patients with significant hyperopia) should be evaluated by an ophthalmologist.

5.10 Increased Intraocular Pressure and Glaucoma

There have been reports of an elevation of intraocular pressure (IOP) associated with methylphenidate treatment [see Adverse Reactions (6.2)].

Prescribe QuilliChew ER to patients with open-angle glaucoma or abnormally increased IOP only if the benefit of treatment is considered to outweigh the risk. Closely monitor QuilliChew ER -treated patients with a history of abnormally increased IOP or open angle glaucoma.

5.11 Motor and Verbal Tics, and Worsening of Tourette’s Syndrome

CNS stimulants, including methylphenidate, have been associated with the onset or exacerbation of motor and verbal tics. Worsening of Tourette’s syndrome has also been reported [see Adverse Reactions (6.2)].

Before initiating QuilliChew ER, assess the family history and clinically evaluate patients for tics or Tourette’s syndrome. Regularly monitor QuilliChew ER-treated patients for the emergence or worsening of tics or Tourette’s syndrome, and discontinue treatment if clinically appropriate.

6 ADVERSE REACTIONS

The following are discussed in more detail in other sections of the labeling:
• Known hypersensitivity to methylphenidate products or other ingredients of QuilliChew ER [see Contraindications (4.1)]
• Hypertensive Crisis When Used Concomitantly with Monoamine Oxidase Inhibitors [see Contraindications (4.2), Drug Interactions (7.1)]
• Abuse, Misuse, and Addiction [see Boxed Warning, Warnings and Precautions (5.1), Drug Abuse and Dependence (9.2, 9.3)]
• Risks to Patients with Serious Cardiac Disease [see Warnings and Precautions (5.2)]
• Increased Blood Pressure and Heart Rate [see Warnings and Precautions (5.3)]
• Psychiatric Adverse Reactions [see Warnings and Precautions (5.4)]
• Priapism [see Warnings and Precautions (5.5)]
• Peripheral Vasculopathy, including Raynaud’s phenomenon [see Warnings and Precautions (5.6)]
• Long-Term Suppression of Growth in Pediatric Patients [see Warnings and Precautions (5.7)]
• Risks in Phenylketonuria [see Warnings and Precautions (5.8)]
• Acute Angle Closure Glaucoma [see Warnings and Precautions (5.9)]
• Increased Intraocular Pressure and Glaucoma [see Warnings and Precautions (5.10)]
• Motor and Verbal Tics, and Worsening of Tourette’s Syndrome [see Warnings and Precautions (5.11)]

6.1 Clinical Trials Experience

Because clinical trials are conducted under widely varying conditions, adverse reaction rates observed in the clinical trials of a drug cannot be directly compared to rates in the clinical trials of another drug and may not reflect the rates observed in clinical practice.

Adverse Reactions in Studies with Other Methylphenidate Products in Children, Adolescents, and Adults with ADHD

Commonly reported (≥2% of the methylphenidate group and at least twice the rate of the placebo group) adverse reactions from placebo-controlled trials of methylphenidate products include: appetite decreased, weight decreased, nausea, abdominal pain, dyspepsia, dry mouth, vomiting, insomnia, anxiety, nervousness, restlessness, affect lability, agitation, irritability, dizziness, vertigo, tremor, blurred vision, blood pressure increased, heart rate increased, tachycardia, palpitations, hyperhidrosis, and pyrexia.

Adverse Reactions in Studies with QuilliChew ER in Children with ADHD

There is limited experience with QuilliChew ER in controlled trials. The safety data in this section is based on data from a laboratory classroom study conducted in 90 pediatric subjects (ages 6 to 12 years) with ADHD. The study consisted of a 6-week dose optimization period, followed by a randomized, double-blind, parallel group treatment period with the individually optimized dose of QuilliChew ER or placebo.

The most common (≥2% in the QuilliChew ER group and greater than placebo) adverse reactions reported in the double-blind, randomized, placebo-controlled phase in patients optimized to doses of QuilliChew ER 20 to 60 mg/day are described in Table 1.

Table 1: Common Adverse Reactions Occurring in ≥2% of Subjects on QuilliChew ER and Greater than Placebo During the Double-Blind Period of the ADHD Laboratory Classroom Study
Adverse reaction | QuilliChew ER N= 42 n (%) | Placebo N= 44 n (%)
Decreased appetite | 1 (2.4) | 0 (0)
Aggression | 1 (2.4) | 0 (0)
Emotional poverty | 1 (2.4) | 0 (0)
Nausea | 1 (2.4) | 0 (0)
Headache | 1 (2.4) | 0 (0)
Weight decreased | 1 (2.4) | 0 (0)

6.2 Postmarketing Experience

The following adverse reactions have been identified during post approval use of methylphenidate products. Because these reactions are reported voluntarily from a population of uncertain size, it is not possible to reliably estimate their frequency or establish a causal relationship to drug exposure. These adverse reactions are as follows:

Blood and Lymphatic System Disorders: Pancytopenia, Thrombocytopenia, Thrombocytopenic purpura

Cardiac Disorders: Angina pectoris, Bradycardia, Extrasystole, Supraventricular tachycardia, Ventricular extrasystole

Eye Disorders: Diplopia, Increased intraocular pressure, Mydriasis, Visual impairment

General Disorders: Chest pain, Chest discomfort, Hyperpyrexia

Hepatobiliary Disorders: Severe hepatocellular injury

Immune System Disorders: Hypersensitivity reactions such as Angioedema, Anaphylactic reactions, Auricular swelling, Bullous conditions, Exfoliative conditions, Urticarias, Pruritus NEC, Rashes, Eruptions, and Exanthemas NEC

Investigations: Alkaline phosphatase increased, Bilirubin increased, Hepatic enzyme increased, Platelet count decreased, White blood cell count abnormal

Musculoskeletal, Connective Tissue and Bone Disorders: Arthralgia, Myalgia, Muscle twitching, Rhabdomyolysis

Nervous System Disorders: Convulsion, Grand mal convulsion, Dyskinesia, Serotonin syndrome in combination with serotonergic drugs, Motor and Verbal Tics

Psychiatric Disorders: Disorientation, Hallucination, Hallucination auditory, Hallucination visual, Libido changes, Mania

Urogenital System: Priapism

Skin and Subcutaneous Tissue Disorders: Alopecia, Erythema

Vascular Disorders: Raynaud’s phenomenon

7 DRUG INTERACTIONS

7.1 Clinically Important Drug Interactions

MAOI Inhibitors
Do not administer QuilliChew ER concomitantly with monoamine oxidase inhibitors (MAOIs) or within 14 days after discontinuing MAOI treatment. Concomitant use of MAOIs and CNS stimulants can cause hypertensive crisis. Potential outcomes include death, stroke, myocardial infarction, aortic dissection, ophthalmological complications, eclampsia, pulmonary edema, and renal failure.

Antihypertensive Drugs
QuilliChew ER may decrease the effectiveness of drugs used to treat hypertension. Monitor blood pressure and adjust the dosage of the hypertensive drug as needed [see Warnings and Precautions (5.3)].

Halogenated Anesthetics
Concomitant use of halogenated anesthetics and QuilliChew ER may increase the risk of sudden blood pressure and heart rate increase during surgery. Avoid use of QuilliChew ER in patients being treated with anesthetics on the day of surgery.

Risperidone
Combined use of methylphenidate with risperidone when there is a change, whether an increase or decrease, in dosage of either or both medications, may increase the risk of extrapyramidal symptoms (EPS). Monitor for signs of EPS.

8 USE IN SPECIFIC POPULATIONS

8.1 Pregnancy

Pregnancy Exposure Registry

There is a pregnancy exposure registry that monitors pregnancy outcomes in women exposed to ADHD medications during pregnancy. Healthcare providers are encouraged to register patients by calling the National Pregnancy Registry for Psychostimulants at 1-866-961-2388 or visiting online at https://womensmentalhealth.org/clinical-and-research-programs/pregnancyregistry/othermedications/.

Risk Summary

There are limited published studies and small case series that report on the use of methylphenidate in pregnant women; however, the data are insufficient to inform any drug-associated risks. There are clinical considerations [see Clinical Considerations]. No teratogenic effects were observed in embryo-fetal development studies with oral administration of methylphenidate to pregnant rats and rabbits during organogenesis at doses 2 and 11 times, respectively, the maximum recommended human dose (MRHD). However, spina bifida was observed in rabbits at a dose 40 times the MRHD [see Data].

In the U.S. general population, the estimated background risk of major birth defects and miscarriage in clinically recognized pregnancies is 2% to 4% and 15% to 20%, respectively.

Clinical Considerations

Fetal/Neonatal adverse reactions

CNS stimulant medications, such as QuilliChew ER, can cause vasoconstriction and thereby decrease placental perfusion. No fetal and/or neonatal adverse reactions have been reported with the use of therapeutic doses of methylphenidate during pregnancy; however, premature delivery and low birth weight infants have been reported in amphetamine-dependent mothers.

Data

Animal Data

In studies conducted in rats and rabbits, methylphenidate was administered orally at doses of up to 75 and 200 mg/kg/day, respectively, during the period of organogenesis. Teratogenic effects (increased incidence of fetal spina bifida) were observed in rabbits at the highest dose, which is approximately 40 times the maximum recommended human dose (MRHD) on a mg/m^2 basis. The no effect level for embryo-fetal development in rabbits was 60 mg/kg/day (11 times the MRHD on a mg/m^2 basis). There was no evidence of specific teratogenic activity in rats, although increased incidences of fetal skeletal variations were seen at the highest dose level (7 times the MRHD on a mg/m^2 basis), which was also maternally toxic. The no effect level for embryo-fetal development in rats was 25 mg/kg/day (2 times the MRHD on a mg/m^2 basis).

8.2 Lactation

Risk Summary

Limited published literature reports that methylphenidate is present in human milk, which resulted in infant doses of 0.16% to 0.7% of the maternal weight-adjusted dosage and a milk/plasma ratio ranging between 1.1 and 2.7. There are no reports of adverse effects on the breastfed infant and no effects on milk production. Long-term neurodevelopmental effects on infants from CNS stimulant exposure are unknown. The developmental and health benefits of breastfeeding should be considered along with the mother's clinical need for QuilliChew ER and any potential adverse effects on the breastfed infant from QuilliChew ER or from the underlying maternal condition.

Clinical Considerations

Monitor breastfeeding infants for adverse reactions, such as agitation, insomnia, anorexia, and reduced weight gain.

8.4 Pediatric Use

The safety and effectiveness of QuilliChew ER have not been established in pediatric patients below the age of 6 years.

In studies evaluating extended-release methylphenidate products, patients 4 to <6 years of age had higher systemic methylphenidate exposures than those observed in older pediatric patients at the same dosage. Pediatric patients 4 to <6 years of age also had a higher incidence of adverse reactions, including weight loss.

The safety and effectiveness of QuilliChew ER have been established in pediatric patients ages 6 to 17 years. Use of QuilliChew ER in these age groups is based on one adequate and well-controlled clinical study in pediatric patients 6 to 12 years old, pharmacokinetic data in adolescents and adults, and safety information from other methylphenidate-containing products.

Long Term Suppression of Growth

Growth should be monitored during treatment with CNS stimulants, including QuilliChew ER. Children who are not growing or gaining weight as expected may need to have their treatment interrupted [see Warnings and Precautions (5.7)].

Juvenile Animal Data

Rats treated with methylphenidate early in the postnatal period through sexual maturation demonstrated a decrease in spontaneous locomotor activity in adulthood. A deficit in acquisition of a specific learning task was observed in females only. The doses at which these findings were observed are at least 6 times the maximum recommended human dose (MRHD) on a mg/m^2 basis.

In the study conducted in young rats, methylphenidate was administered orally at doses of up to 100 mg/kg/day for 9 weeks, starting early in the postnatal period (postnatal day 7) and continuing through sexual maturity (postnatal week 10). When these animals were tested as adults (postnatal weeks 13 to 14), decreased spontaneous locomotor activity was observed in males and females previously treated with 50 mg/kg/day (approximately 6 times the maximum recommended human dose [MRHD] on a mg/m^2 basis) or greater, and a deficit in the acquisition of a specific learning task was observed in females exposed to the highest dose (12 times the MRHD on a mg/m^2 basis). The no effect level for juvenile neurobehavioral development in rats was 5 mg/kg/day (half the MRHD on a mg/m^2 basis). The clinical significance of the long-term behavioral effects observed in rats is unknown.

8.5 Geriatric Use

QuilliChew ER has not been studied in patients over the age of 65 years.

9 DRUG ABUSE AND DEPENDENCE

9.1 Controlled Substance

QuilliChew ER contains methylphenidate, a Schedule II controlled substance.

9.2 Abuse

QuilliChew ER has a high potential for abuse and misuse which can lead to the development of a substance use disorder, including addiction [see Warnings and Precautions (5.1)].
QuilliChew ER can be diverted for non-medical use into illicit channels or distribution.

Abuse is the intentional non-therapeutic use of a drug, even once, to achieve a desired psychological or physiological effect. Misuse is the intentional use, for therapeutic purposes, of a drug by an individual in a way other than prescribed by a health care provider or for whom it was not prescribed. Drug addiction is a cluster of behavioral, cognitive, and physiological phenomena that may include a strong desire to take the drug, difficulties in controlling drug use (e.g., continuing drug use despite harmful consequences, giving a higher priority to drug use than other activities and obligations), and possible tolerance or physical dependence.

Misuse and abuse of methylphenidate may cause increased heart rate, respiratory rate, or blood pressure; sweating; dilated pupils; hyperactivity; restlessness; insomnia; decreased appetite; loss of coordination; tremors; flushed skin; vomiting; and/or abdominal pain. Anxiety, psychosis, hostility, aggression, and suicidal or homicidal ideation have also been observed with CNS stimulants abuse and/or misuse. Misuse and abuse of CNS stimulants, including QuilliChew ER, can result in overdose and death [see Overdosage (10)], and this risk is increased with higher doses or unapproved methods of administration, such as snorting or injection.

9.3 Dependence

Physical Dependence
QuilliChew ER may produce physical dependence. Physical dependence is a state that develops as a result of physiological adaptation in response to repeated drug use, manifested by withdrawal signs and symptoms after abrupt discontinuation or a significant dose reduction of a drug.

Withdrawal signs and symptoms after abrupt discontinuation or dose reduction following prolonged use of CNS stimulants including QuilliChew ER include dysphoric mood; depression; fatigue; vivid, unpleasant dreams; insomnia or hypersomnia; increased appetite; and psychomotor retardation or agitation.
Tolerance
QuilliChew ER may produce tolerance. Tolerance is a physiological state characterized by a reduced response to a drug after repeated administration (i.e., a higher dose of a drug is required to produce the same effect that was once obtained at a lower dose).

10 OVERDOSAGE

Clinical Effects of Overdose

Overdose of CNS stimulants is characterized by the following sympathomimetic effects:

- Cardiovascular effects including tachyarrhythmias, and hypertension or hypotension. Vasospasm, myocardial infarction, or aortic dissection may precipitate sudden cardiac death. Takotsubo cardiomyopathy may develop.
- CNS effects including psychomotor agitation, confusion, and hallucinations. Serotonin syndrome, seizures, cerebral vascular accidents, and coma may occur.
- Life-threatening hyperthermia (temperatures greater than 104°F) and rhabdomyolysis may develop.

Overdose Management
Consider the possibility of multiple drug ingestion. The pharmacokinetic profile of QuilliChew ER should be considered when treating patients with overdose. Because methylphenidate has a large volume of distribution and is rapidly metabolized, dialysis is not useful. Consider contacting the Poison Help line (1-800-222-1222) or a medical toxicologist for additional overdose management recommendations.

11 DESCRIPTION

QuilliChew ER (methylphenidate hydrochloride extended-release chewable tablets) is available in three dosage strengths - 20 mg, 30 mg and 40 mg. The dosage strengths are expressed in terms of methylphenidate hydrochloride equivalents; however only 15% of methylphenidate is present as methylphenidate hydrochloride salt. The remaining 85% is present as methylphenidate ionically-bound to the sulfonate groups of sodium polystyrene sulfonate particles. QuilliChew ER contains approximately 30% immediate-release and 70% extended-release methylphenidate.

The QuilliChew ER extended-release chewable tablets are cherry flavored.

Methylphenidate HCl is a central nervous system (CNS) stimulant. The chemical name is methyl α- phenyl-2-piperidineacetate hydrochloride, and its structural formula is shown in Figure 1.

Figure 1: Methylphenidate HCl Structure

Methylphenidate HCl is a white, odorless crystalline powder. Its solutions are acid to litmus. It is freely soluble in water and in methanol, soluble in alcohol, and slightly soluble in chloroform and in acetone.

QuilliChew ER also contains the following inactive ingredients: aspartame [see Warnings and Precautions (5.8)], cherry flavor, citric acid, crospovidone, D&C red #30 (for 30 mg strength), D&C red #7 (for 40 mg strength), guar gum, magnesium stearate, mannitol, microcrystalline cellulose, polyvinyl acetate, polyvinyl alcohol, povidone, silicon dioxide, sodium polystyrene sulfonate, talc, triacetin, xanthan gum.

12 CLINICAL PHARMACOLOGY

12.1 Mechanism of Action

Methylphenidate HCl is a central nervous system (CNS) stimulant.

12.2 Pharmacodynamics

Methylphenidate is a racemic mixture comprised of the d- and l-isomers. The d-isomer is more pharmacologically active than the l-isomer. The mode of therapeutic action in ADHD is not known. Methylphenidate blocks the reuptake of norepinephrine and dopamine into the presynaptic neuron and increases the release of these monoamines into the extraneuronal space.

12.3 Pharmacokinetics

Absorption

Following a single oral dose of 40 mg QuilliChew ER under fasting conditions, plasma methylphenidate reached maximal concentration (Cmax) at a median time of 5 hours after dosing. Compared to an immediate-release formulation of methylphenidate chewable tablet (40 mg in 2 equal doses of 20 mg, 6 hours apart), methylphenidate mean peak concentration and exposure (AUCinf) was about 20% and 11% lower, respectively, after single dose administration of 40 mg QuilliChew ER (Figure 2).

Figure 2: Mean Methylphenidate Plasma Concentration-Time Profiles After Administration of 40 mg QuilliChew ER or Methylphenidate Immediate-Release Chewable Tablets (IRCT, 2 Equal Doses of 20 mg, 6 Hours Apart) Under Fasted Conditions in Healthy Volunteers

Food Effect

High-fat meal had no effect on the time to peak concentration, and increased Cmax and systemic exposure (AUCinf) of methylphenidate by about 20% and 4%, respectively, after a single dose administration of 40 mg QuilliChew ER.

Elimination

Plasma methylphenidate concentrations decline monophasically following oral administration of QuilliChew ER. The mean plasma terminal elimination half-life of methylphenidate was about 5.2 hours in healthy volunteers following a single 40 mg dose administration.

Metabolism

In humans, methylphenidate is metabolized primarily via de-esterification to alpha-phenyl-piperidine acetic acid (PPAA). The metabolite has little or no pharmacologic activity.

Excretion

After oral dosing of radiolabeled methylphenidate in humans, about 90% of the radioactivity was recovered in urine. The main urinary metabolite was PPAA, accounting for approximately 80% of the dose.

Alcohol Effect

At 40% alcohol concentration, there was about 90% release methylphenidate from QuilliChew ER 40 mg tablet within half an hour. The results with the 40 mg chewable tablet strength are considered representative of the other available tablet strengths.

Specific Populations

Sex

There is insufficient experience with the use of QuilliChew ER to detect gender variations in pharmacokinetics.

Race

There is insufficient experience with the use of QuilliChew ER to detect ethnic variations in pharmacokinetics.

Age

There are no specific pediatric pharmacokinetic studies for QuilliChew ER. However, the pharmacokinetics of methylphenidate in pediatric patients 6 to 17 years old are not expected to be significantly different from adults following QuilliChew ER administration.

Renal Impairment

There is no experience with the use of QuilliChew ER in patients with renal insufficiency. After oral administration of radiolabeled methylphenidate in humans, methylphenidate was extensively metabolized and approximately 80% of the radioactivity was excreted in the urine in the form of PPAA. Since renal clearance is not an important route of methylphenidate clearance, renal insufficiency is expected to have little effect on the pharmacokinetics of QuilliChew ER.

Hepatic Impairment

There is no experience with the use of QuilliChew ER in patients with hepatic insufficiency.

13 NONCLINICAL TOXICOLOGY

13.1 Carcinogenesis, Mutagenesis, Impairment of Fertility

Carcinogenesis

In a lifetime carcinogenicity study carried out in B6C3F1 mice, methylphenidate caused an increase in hepatocellular adenomas and, in males only, an increase in hepatoblastomas, at a daily dose of approximately 60 mg/kg/day. This dose is approximately 4 times the maximum recommended human dose on a mg/m^2 basis. Hepatoblastoma is a relatively rare rodent malignant tumor type. There was no increase in total malignant hepatic tumors. The mouse strain used is sensitive to the development of hepatic tumors, and the significance of these results to humans is unknown.

Methylphenidate did not cause any increase in tumors in a lifetime carcinogenicity study carried out in F344 rats; the highest dose used was approximately 45 mg/kg/day, which is approximately 5 times the maximum recommended human dose on a mg/m^2 basis.

Mutagenesis

Methylphenidate was not mutagenic in the in vitro Ames reverse mutation assay or in the in vitro mouse lymphoma cell forward mutation assay. Sister chromatid exchanges and chromosome aberrations were increased, indicative of a weak clastogenic response, in an in vitro assay in cultured Chinese Hamster Ovary (CHO) cells. Methylphenidate was negative in an in vivo mouse bone marrow micronucleus assay.

Impairment of Fertility

Methylphenidate did not impair fertility in male or female mice that were fed diets containing the drug in an 18-week Continuous Breeding study. The study was conducted at doses of up to 160 mg/kg/day, approximately 8-fold the maximum recommended human dose on a mg/m^2 basis.

14 CLINICAL STUDIES

The efficacy of QuilliChew ER was evaluated in a laboratory classroom study conducted in 90 pediatric subjects (ages 6 to 12 years) with ADHD. Patients in the trial met DSM-IV criteria for ADHD. The study began with a 6-week open-label dose optimization period with an initial QuilliChew ER dose of 20 mg. Patients were instructed to chew each dose once daily in the morning. The dose could be titrated weekly in increments of 10 to 20 mg until a therapeutic dose or the maximum dose of 60 mg/day was reached.

Eighty-six of the 90 enrolled subjects then entered a 1-week randomized, double-blind, parallel group treatment period with the individually optimized dose of QuilliChew ER or placebo. The intent-to-treat (ITT) population consisted of 85 randomized subjects who received at least 1 dose of double-blind study drug and had at least 1 post-Baseline assessment of the primary efficacy variable. At the end of the double-blind treatment period, the laboratory classroom raters and teachers evaluated the attention and behavior of the subjects, throughout the day using the Swanson, Kotkin, Agler, M-Flynn, and Pelham (SKAMP) rating scale. The SKAMP rating scale is a validated 13-item teacher-rated scale that assesses manifestations of ADHD in a classroom setting.

The SKAMP-Combined score, measured at 0.75, 2, 4, 8, 10, 12, and 13 hours post-dose during the laboratory classroom day at the end of the double-blind treatment period, was used to assess the primary and the key secondary efficacy parameters. The primary efficacy endpoint was the average of treatment effects across all the time points as specified above during the classroom day. The key secondary efficacy parameters were onset and duration of clinical effect. QuilliChew ER was statistically significantly superior to placebo with respect to the primary endpoint (Table 2). QuilliChew ER also showed improvement over placebo at 0.75, 2, 4, and 8 hours post-dosing. Efficacy results at each time point are summarized in Figure 3.

Table 2: Primary Efficacy Result (ITT Population)
Study Number | Treatment Group | Primary Efficacy measure: Average of Treatment Effect Across All Time Points Based on SKAMP-Combined Score
 |  | Mean Pre-Dose Score on Classroom Day (SD) | LS Mean (SE) for the Classroom day | Placebo-subtracted Differencea (95% CI)
Study 1 | Quillichew ER (N=42) | 17.5 (11.6) | 12.1 (1.4) | -7.0 (-10.9, -3.1)
 | Placebo (N-43) | 13.8 (10.0) | 19.1 (1.4)

N: number of patients; SD: standard deviation; SE: standard error; LS Mean: least-squares

mean; CI: confidence interval.

aLeast-Squares Mean Difference (drug minus placebo).

Figure 3: SKAMP-Combined Scores Over Time (LS Mean ±SE) by Treatment Group (ITT Population)

ITT: intent-to-treat

LS means from post-dose time-points were obtained from a repeated measures mixed model with terms for center, hour, treatment and treatment by hour interaction. For the pre-dose time-point, arithmetic means and standard errors are displayed.

16 HOW SUPPLIED/STORAGE AND HANDLING

16.1 How Supplied

QuilliChew ER is supplied as extended-release chewable tablets in 20 mg, 30 mg and 40 mg strengths.

The 20 mg strength extended-release chewable tablet is available as a speckled, off-white, capsule-shaped coated tablet, debossed with "NP 12" on one side and functionally scored on the other side.

The 30 mg strength extended-release chewable tablet is available as a speckled, light pink color, capsule-shaped coated tablet, debossed with "NP 13" on one side and functionally scored on the other side.

The 40 mg strength extended-release chewable tablet is available as a speckled, dark pink to peach color, capsule-shaped coated tablet, debossed with "NP 14" on one side and plain on the other side (not scored).

The product is supplied in bottles of 30 and 100.

QuilliChew ER extended-release chewable tablets
Package Configuration | Tablet Strength (mg) | NDC | Print
Bottles of 30 | 20 mg | NDC 24478‑074‑02 | NP 12
Bottles of 100 | 20 mg | NDC-24478-074-01 | NP 12
Bottles of 30 | 30 mg | NDC 24478‑075‑02 | NP 13
Bottles of 100 | 30 mg | NDC-24478-075-01 | NP 13
Bottles of 30 | 40 mg | NDC 24478‑076‑02 | NP 14
Bottles of 100 | 40 mg | NDC-24478-076-01 | NP 14

16.2 Storage and Handling

Store at 20ºC to 25ºC (68ºF to 77ºF); excursions permitted from 15ºC to 30ºC (59ºF to 86ºF). [See USP Controlled Room Temperature.]

17 PATIENT COUNSELING INFORMATION

Advise patients to read the FDA-approved patient labeling (Medication Guide).

Abuse, Misuse and Addiction
Educate patients and their families about the risks of abuse, misuse, and addiction of QuilliChew ER, which can lead to overdose and death, and proper disposal of any unused drug [see Warnings and Precautions (5.1), Drug Abuse and Dependence (9.2), Overdosage (10)].
Advise patients to store QuilliChew ER in a safe place, preferably locked, and instruct patients to not give QuilliChew ER to anyone else.

Dosage and Administration Instructions
Advise patients that QuilliChew ER should be taken by mouth once daily in the morning with or without food.

Risks to Patients with Serious Cardiac Disease
Advise patients that there are potential risks to patients with serious cardiac disease, including sudden death, with QuilliChew ER use. Instruct patients to contact a health care provider immediately if they develop symptoms such as exertional chest pain, unexplained syncope, or other symptoms suggestive of cardiac disease [see Warnings and Precautions (5.2)].

Increased Blood Pressure and Heart Rate
Advise patients that QuilliChew ER can elevate blood pressure and heart rate [see Warnings and Precautions (5.3)].

Psychiatric Adverse Reactions
Advise patients that QuilliChew ER, at recommended doses, can cause psychotic or manic symptoms, even in patients without a prior history of psychotic symptoms or mania [see Warnings and Precautions (5.4)].

Priapism
Advise patients, caregivers, and family members of the possibility of painful or prolonged penile erections (priapism). Instruct the patient to seek immediate medical attention in the event of priapism [see Warnings and Precautions (5.5)].

Circulation Problems in Fingers and Toes [Peripheral Vasculopathy, including Raynaud’s Phenomenon]

- Instruct patients beginning treatment with QuilliChew ER about the risk of peripheral vasculopathy, including Raynaud’s phenomenon, and associated signs and symptoms: fingers or toes may feel numb, cool, painful, and/or may change color from pale, to blue, to red.
- Instruct patients to report to their physician any new numbness, pain, skin color change, or sensitivity to temperature in fingers or toes.
- Instruct patients to call their physician immediately with any signs of unexplained wounds appearing on fingers or toes while taking QuilliChew ER.
- Further clinical evaluation (e.g., rheumatology referral) may be appropriate for certain patients [see Warnings and Precautions (5.6)].

Long-Term Suppression of Growth in Pediatric Patients
Advise patients, families, and caregivers that QuilliChew ER can cause slowing of growth and weight loss [see Warnings and Precautions (5.7)].

Alcohol Effect
Advise patients to avoid alcohol while taking QuilliChew ER extended-release chewable tablets. Consumption of alcohol while taking QuilliChew ER may result in a more rapid release of the dose of methylphenidate [see Clinical Pharmacology (12.3)].

Risks in Patients with Phenylketonuria (PKU)
Advise patients with phenylketonuria that QuilliChew ER extended-release chewable tablets contain phenylalanine, a component of aspartame [see Warnings and Precautions (5.8)].

Increased Intraocular Pressure (IOP) and Glaucoma
Advise patients that IOP and glaucoma may occur during treatment with QuilliChew ER [see Warnings and Precautions (5.9)].
Motor and Verbal Tics, and Worsening of Tourette’s Syndrome
Advise patients that motor and verbal tics and worsening of Tourette’s Syndrome may occur during treatment with QuilliChew ER. Instruct patients to notify their healthcare provider if emergence of new tics or worsening of tics or Tourette’s syndrome occurs [see Warnings and Precautions (5.10)].
Pregnancy Registry
Advise patients that there is a pregnancy exposure registry that monitors pregnancy outcomes in females exposed to QuilliChew ER during pregnancy [see Use in Specific Populations (8.1)].
Lactation
Advise nursing mother to monitor infants exposed to QuilliChew ER through breastmilk for agitation, poor feeding, and reduced weight gain [see Use in Specific Populations (8.2)].

This product’s label may have been updated. For current full prescribing information, please visit www.trispharma.com.

Distributed by:

Manufactured by:

Tris Pharma, Inc.

Monmouth Junction, NJ 08852

LB8533

Rev. 06

MEDICATION GUIDE

QuilliChew ER® (quil-ih' CHOO' ee-ahr)

(methylphenidate hydrochloride)

extended-release chewable tablets CII

What is the most important information I should know about QuilliChew ER?

QuilliChew ER may cause serious side effects, including:

- Abuse, misuse, and addiction. QuilliChew ER has a high chance for abuse and misuse and may lead to substance use problems, including addiction. Misuse and abuse of QuilliChew ER, other methylphenidate containing medicines, and amphetamine containing medicines, can lead to overdose and death. The risk of overdose and death is increased with higher doses of QuilliChew ER or when it is used in ways that are not approved, such as snorting or injection.

- Your healthcare provider should check you or your child’s risk for abuse, misuse, and addiction before starting treatment with QuilliChew ER and will monitor you or your child during treatment.
- QuilliChew ER may lead to physical dependence after prolonged use, even if taken as directed by your healthcare provider.
- Do not give QuilliChew ER to anyone else. See “What is QuilliChew ER?” for more information.
- Keep QuilliChew ER in a safe place and properly dispose of any unused medicine. See “How should I store QuilliChew ER?” for more information.
- Tell your healthcare provider if you or your child have ever abused or been dependent on alcohol, prescription medicines, or street drugs.

- Risks for people with serious heart disease. Sudden death has happened in people who have heart defects or other serious heart disease.

Your healthcare provider should check you or your child carefully for heart problems before starting QuilliChew ER.

Tell your healthcare provider if you or your child have any heart disease, or heart defects.

Call your healthcare provider or go to the nearest hospital emergency room right away if you or your child has any signs of heart problems such as chest pain, shortness of breath, or fainting while taking QuilliChew ER.

- Increased blood pressure and heart rate.

Your health care provider should check your or your child’s blood pressure and heart rate regularly during treatment with QuilliChew ER.

Mental (Psychiatric) problems:

- new or worse behavior and thought problems
- new or worse bipolar illness
- new psychotic symptoms (such as hearing voices, believing things that are not true, are suspicious) or new manic symptoms

Tell your healthcare provider about any mental problems you or your child have, or about a family history of suicide, bipolar illness, or depression.

Call your healthcare provider right away if you or your child have any new or worsening mental symptoms or problems while taking QuilliChew ER, especially seeing or hearing things that are not real, believing things that are not real, or are suspicious.

What is QuilliChew ER?

QuilliChew ER is a central nervous system stimulant prescription medicine. QuilliChew ER is an extended-release chewable tablet. It is used for the treatment of Attention Deficit Hyperactivity Disorder (ADHD). QuilliChew ER may help increase attention and decrease impulsiveness and hyperactivity in people with ADHD.

QuilliChew ER is not recommended for use in children under 6 years of age with ADHD.

QuilliChew ER is a federally controlled substance (CII) because it contains methylphenidate that can be a target for people who abuse prescription medicines or street drugs. Keep QuilliChew ER in a safe place to protect it from theft. Never give your QuilliChew ER to anyone else, because it may cause death or harm them. Selling or giving away QuilliChew ER may harm others and is against the law.

Do not take QuilliChew ER if you or your child:

- are allergic to methylphenidate hydrochloride, or any of the ingredients in QuilliChew ER. See the end of this Medication Guide for a complete list of ingredients in QuilliChew ER.
- are taking or have taken within the past 14 days a type of anti-depression medicine called a monoamine oxidase inhibitor (MAOI).

QuilliChew ER may not be right for you or your child. Before starting QuilliChew ER tell your or your child’s health care provider about all health conditions (or a family history of) including:

- heart problems, heart disease, heart defects, or high blood pressure
- mental problems including psychosis, mania, bipolar illness, or depression
- circulation problems in fingers and toes
- have eye problems, including increased pressure in your eye, glaucoma, or problems with your close-up vision (farsightedness)
- have or had repeated movements or sounds (tics) or Tourette’s syndrome, or have a family history of tics or Tourette’s syndrome
- phenylketonuria (PKU). QuilliChew ER extended-release chewable tablets contain phenylalanine as part of the artificial sweetener, aspartame. The artificial sweetener may be harmful to people with PKU or who are allergic to phenylalanine.
- if you are pregnant or plan to become pregnant. It is not known if QuilliChew ER will harm your unborn baby. Talk to your health care provider if you are pregnant or plan to become pregnant.
  - There is a pregnancy registry for females who are exposed to ADHD medications during pregnancy. The purpose of the registry is to collect information about the health of females exposed to Quillichew ER and their baby. If you or your child becomes pregnant during treatment with Quillichew ER, talk to your healthcare provider about registering with the National Pregnancy Registry for Psychostimulants at 1-866-961-2388 or visit https://womensmentalhealth.org/clinical-and-research-programs/pregnancyregistry/othermedications/.
- if you are breastfeeding or plan to breast feed. QuilliChew ER passes into your breast milk. You and your healthcare provider should decide if you will take QuilliChew ER or breastfeed.

Tell your healthcare provider about all of the medicines that you or your child take including prescription and nonprescription medicines, vitamins, and herbal supplements. QuilliChew ER and some medicines may interact with each other and cause serious side effects. Sometimes the doses of other medicines will need to be adjusted while taking QuilliChew ER.

Your healthcare provider will decide whether QuilliChew ER can be taken with other medicines.

Especially tell your healthcare provider if you or your child takes:

- anti-depression medicines including MAOIs

Know the medicines that you or your child takes. Keep a list of your medicines with you to show your health care provider and pharmacist.

Do not start any new medicine while taking QuilliChew ER without talking to your healthcare provider first.

How should QuilliChew ER be taken?

- Read the step-by-step instructions for using QuilliChew ER extended-release chewable tablets at the end of this Medication Guide.
- Take QuilliChew ER exactly as prescribed. Your healthcare provider may adjust the dose, if needed, until it is right for you or your child. During dose adjustment, you or your child may still have ADHD symptoms.
- Take QuilliChew ER 1 time each day in the morning. QuilliChew ER is an extended-release chewable tablet that releases medicine into your body throughout the day.
- The 20 mg and 30 mg QuilliChew ER chewable tablets are scored (bisected) and can be cut in half if needed, for you to get the right dose. QuilliChew ER 40mg is not scored (bisected) and cannot be divided.
- QuilliChew ER can be taken with or without food.
- Your healthcare provider may do regular checks of the blood, heart, and blood pressure while taking QuilliChew ER.
- Children should have their height and weight checked often while taking QuilliChew ER.
- If a dose is missed, you or your child should talk to your health care provider about dosing.

If you or your child take too much QuilliChew ER, call your healthcare provider or Poison Help line at 1-800-222-1222 or go to the nearest hospital emergency room right away.

What should I avoid while taking QuilliChew ER?

- QuilliChew ER should not be taken with MAOI medicines. Do not start taking QuilliChew ER if you stopped taking an MAOI in the last 14 days.
- Do not drink alcohol while taking QuilliChew ER. This may cause a faster release of your methylphenidate dose.

What are the possible side effects of QuilliChew ER?

QuilliChew ER may cause serious side effects, including:

- See “What is the most important information I should know about QuilliChew ER?” for information on reported heart and mental problems.

Other serious side effects include:

- Painful and prolonged erections (priapism) have occurred with methylphenidate. If you or your child develop priapism seek medical help right away. Because priapism can cause long lasting damage, it should be checked by a health care provider right away.
- Circulation problems in fingers and toes (peripheral vasculopathy, including Raynaud’s phenomenon). Signs and symptoms may include:

- fingers or toes may feel numb, cool, painful
- fingers or toes may change color from pale, to blue, to red

Tell your healthcare provider if you or your child have numbness, pain, skin color change, or sensitivity to temperature in your fingers or toes, or if you or your child have any signs of unexplained wounds appearing on fingers or toes during treatment with QuilliChew ER.

- Slowing of growth (height and weight) in children. Children should have their height and weight checked often during treatment with QuilliChew ER. QuilliChew ER treatment may be stopped if your child is not gaining weight or height.
- Eye problems (increased pressure in the eye and glaucoma). Call your healthcare provider right away if you or your child develop changes in your vision or eye pain, swelling, or redness.
- New or worsening tics or worsening Tourette’s syndrome. Tell your healthcare provider if you or your child get any new or worsening tics or worsening Tourette’s syndrome during treatment with QuilliChew ER.

The most common side effects of QuilliChew ER include:

- decreased appetite
- trouble sleeping
- nausea
- vomiting
- irritability
- indigestion
- stomach pain
- weight loss
- anxiety
- dizziness
- irritability
- mood swings
- fast heart beat
- increased blood pressure

These are not all the possible side effects of QuilliChew ER.

Call your doctor for medical advice about side effects. You may report side effects to FDA at 1-800-FDA-1088.

How should I store QuilliChew ER?

- Store QuilliChew ER in a safe place at 68°F to 77°F (20°C to 25°C).
- Dispose of remaining, unused, or expired QuilliChew ER by a medicine take-back program at a U.S. Drug Enforcement Administration (DEA) authorized collection site. If no take-back program or DEA authorized collector is available, mix QuilliChew ER with an undesirable, nontoxic substance such as dirt, cat litter, or used coffee grounds to make it less appealing to children and pets. Place the mixture in a container such as a sealed plastic bag and throw away QuilliChew ER in the household trash. Visit www.fda.gov/drugdisposal for additional information on disposal of unused medicines.

- Keep QuilliChew ER and all medicines out of the reach of children.

General information about the safe and effective use of QuilliChew ER

Medicines are sometimes prescribed for purposes other than those listed in a Medication Guide. Do not use QuilliChew ER for a condition for which it was not prescribed. Do not give QuilliChew ER to other people, even if they have the same condition. It may harm them.

You can ask your pharmacist or healthcare provider for information about QuilliChew ER that is written for healthcare professionals.

What are the ingredients in QuilliChew ER?

Active Ingredient: methylphenidate

Inactive Ingredients: aspartame, cherry flavor, citric acid, crospovidone, D&C red #30 (for 30 mg strength), D&C red #7 (for 40 mg strength), guar gum, magnesium stearate, mannitol, microcrystalline cellulose, polyvinyl acetate, polyvinyl alcohol, povidone, silicon dioxide, sodium polystyrene sulfonate, talc, triacetin, xanthan gum.

Distributed by:

Manufactured by:

Tris Pharma, Inc., Monmouth Junction, NJ 08852

For more information, please contact Tris Pharma, Inc. at (732) 940-0358 or visit the website at www.QuilliChewER.com.

This product’s label may have been updated. For current full prescribing information, please visit www.trispharma.com.

This Medication Guide has been approved by the U.S. Food and Drug Administration Revised: 09/2025

PRINCIPAL DISPLAY PANEL

NDC 24478-074-02
QUILLICHEW ER
(methylphenidate HCI)
extended-release chewable tablets CII
20 mg
30 Tablets
Rx Only

PRINCIPAL DISPLAY PANEL

NDC 24478-074-01
QUILLICHEW ER
(methylphenidate HCI)
extended-release chewable tablets CII
20 mg
100 Tablets
Rx Only

PRINCIPAL DISPLAY PANEL

NDC 24478-075-02
QUILLICHEW ER
(methylphenidate HCI)
extended-release chewable tablets CII
30 mg
30 Tablets
Rx Only

PRINCIPAL DISPLAY PANEL

NDC 24478-075-01
QUILLICHEW ER
(methylphenidate HCI)
extended-release chewable tablets CII
30 mg
100 Tablets
Rx Only

PRINCIPAL DISPLAY PANEL

NDC 24478-076-02
QUILLICHEW ER
(methylphenidate HCI)
extended-release chewable tablets CII
40 mg
30 Tablets
Rx Only

PRINCIPAL DISPLAY PANEL

NDC 24478-076-01
QUILLICHEW ER
(methylphenidate HCI)
extended-release chewable tablets CII
40 mg
100 Tablets
Rx Only